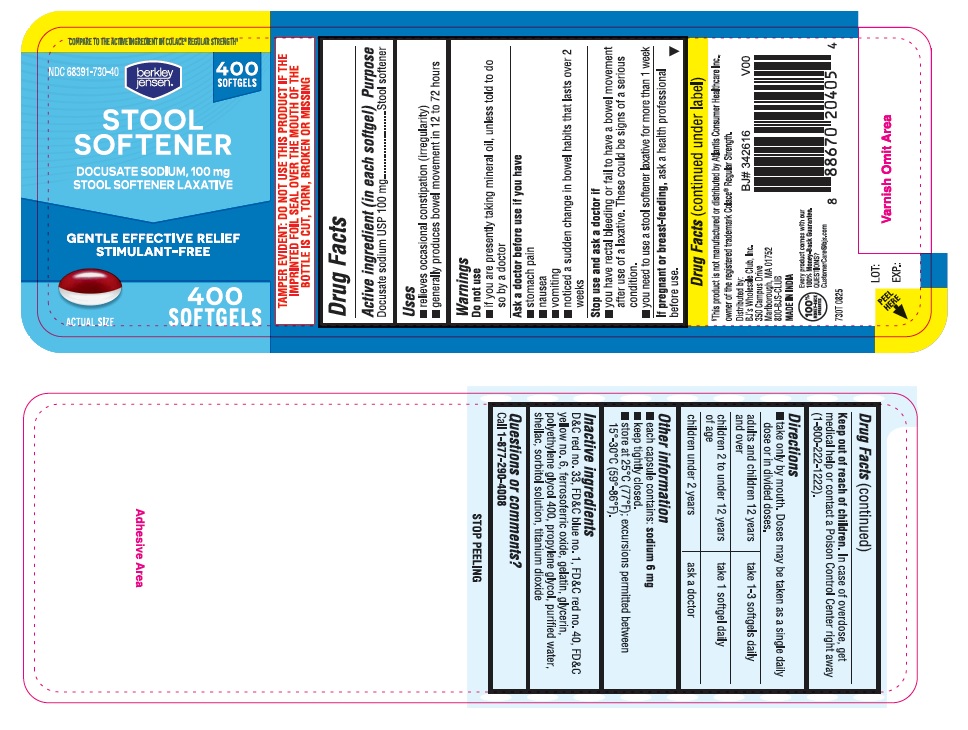 DRUG LABEL: Stool Softener
NDC: 68391-730 | Form: CAPSULE
Manufacturer: BJWC (Berkley & Jensen / BJ's)
Category: otc | Type: HUMAN OTC DRUG LABEL
Date: 20250819

ACTIVE INGREDIENTS: DOCUSATE SODIUM 100 mg/1 1
INACTIVE INGREDIENTS: GLYCERIN; PROPYLENE GLYCOL; WATER; SHELLAC; POLYETHYLENE GLYCOL 400; SORBITOL SOLUTION; FD&C BLUE NO. 1; FD&C RED NO. 40; FD&C YELLOW NO. 6; GELATIN, UNSPECIFIED; D&C RED NO. 33; TITANIUM DIOXIDE; FERROSOFERRIC OXIDE

BJs Docusate Sodium Soft Gelatin Capsules 100 mg Dual Color

Drug Facts

Active ingredient (in each softgel)

Docusate sodium USP 100 mg

Purpose

Stool softener

Uses:

- relieves occasional constipation (irregularity)
- generally produces bowel movement in 12 to 72 hours

Warnings

Do not use

- if you are presently taking mineral oil, unless told to do so by a doctor

Ask a doctor before use if you have

- stomach pain
- nausea
- vomiting
- noticed a sudden change in bowel habits that lasts over 2 weeks

Stop use and ask a doctor if

- you have rectal bleeding or fail to have a bowel movement after use of a laxative. These could be signs of a serious condition.
- you need to use a stool softener laxative for more than 1 week

PREGNANCY OR BREAST FEEDING

If pregnant or breast-feeding, ask a health professional before use.

Keep out of reach of children. In case of overdose, get medical help or contact a Poison Control Center right away (1-800-222-1222).

DOSAGE AND ADMINISTRATION

Directions: take only by mouth. Doses may be taken as a single daily dose or in divided doses.

adults and children 12 years and over

adults and children 12 years and over | take 1-3 softgels daily
children 2 to under 12 years of age | take 1 softgel daily
children under 2 years | ask a doctor

Other information

- each capsule contains: sodium 6 mg
- keep tightly closed.
- store at 25°C (77°F); excursions permitted between 15°-30°C (59°-86°F).

INACTIVE INGREDIENT

Inactive ingredients D&C red no. 33, FD&C blue no. 1, FD&C red no. 40, FD&C yellow no. 6, ferrosoferric oxide, gelatin, glycerin, polyethylene glycol 400, propylene glycol, purified water, shellac, sorbitol solution, titanium dioxide

Questions or comments? Call 1-877-290-4008

PACKAGE LABEL

730T Docusate Sodium 100mg 400ct